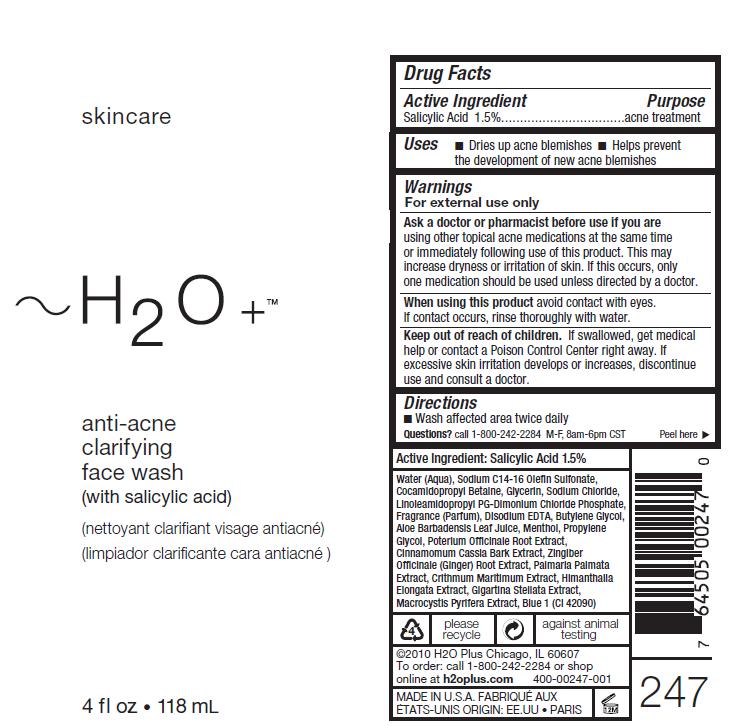 DRUG LABEL: Anti Acne Clarifying Face Wash
NDC: 65903-247 | Form: GEL
Manufacturer: H2O Plus
Category: otc | Type: HUMAN OTC DRUG LABEL
Date: 20110928

ACTIVE INGREDIENTS: Salicylic Acid 15 uL/1 mL
INACTIVE INGREDIENTS: Water; SODIUM C12-14 OLEFIN SULFONATE; COCAMIDOPROPYL BETAINE; GLYCERIN; SODIUM CHLORIDE; LINOLEAMIDOPROPYL PG-DIMONIUM CHLORIDE PHOSPHATE; EDETATE DISODIUM; BUTYLENE GLYCOL; ALOE VERA LEAF; MENTHOL; PROPYLENE GLYCOL; SANGUISORBA OFFICINALIS ROOT; CHINESE CINNAMON; GINGER; CRITHMUM MARITIMUM; HIMANTHALIA ELONGATA; MASTOCARPUS STELLATUS; MACROCYSTIS PYRIFERA

DRUG FACTS

Active Ingredient
Salicylic Acid 1.5%...

Purpose
acne treatment

WARNINGS

For external use only

Ask a doctor or pharmacist before use if you are
using other topical acne medications at the same time
or immediately following use of this product. This may
increase dryness or irritation of skin. If this occurs, only
one medication should be used unless directed by a doctor.

DOSAGE AND ADMINISTRATION

Wash affected area twice daily

When using this product avoid contact with eyes.
If contact occurs, rinse thoroughly with water.

Keep out of reach of children. If swallowed, get medical
help or contact a Poison Control Center right away. If
excessive skin irritation develops or increases, discontinue
use and consult a doctor.

Directions

Wash affected area twice daily

QUESTIONS

Questions? call 1-800-242-2284 M-F, 8am-6pm CST

INACTIVE INGREDIENT

Water (Aqua), Sodium C14-16 Olefin Sulfonate,
Cocamidopropyl Betaine, Glycerin, Sodium Chloride,
Linoleamidopropyl PG-Dimonium Chloride Phosphate,
Fragrance (Parfum), Disodium EDTA, Butylene Glycol,
Aloe Barbadensis Leaf Juice, Menthol, Propylene
Glycol, Poterium Officinale Root Extract,
Cinnamomum Cassia Bark Extract, Zingiber
Officinale (Ginger) Root Extract, Palmaria Palmata
Extract, Crithmum Maritimum Extract, Himanthalia
Elongata Extract, Gigartina Stellata Extract,
Macrocystis Pyrifera Extract, Blue 1 (CI 42090)

Image of label aacf247.jpg